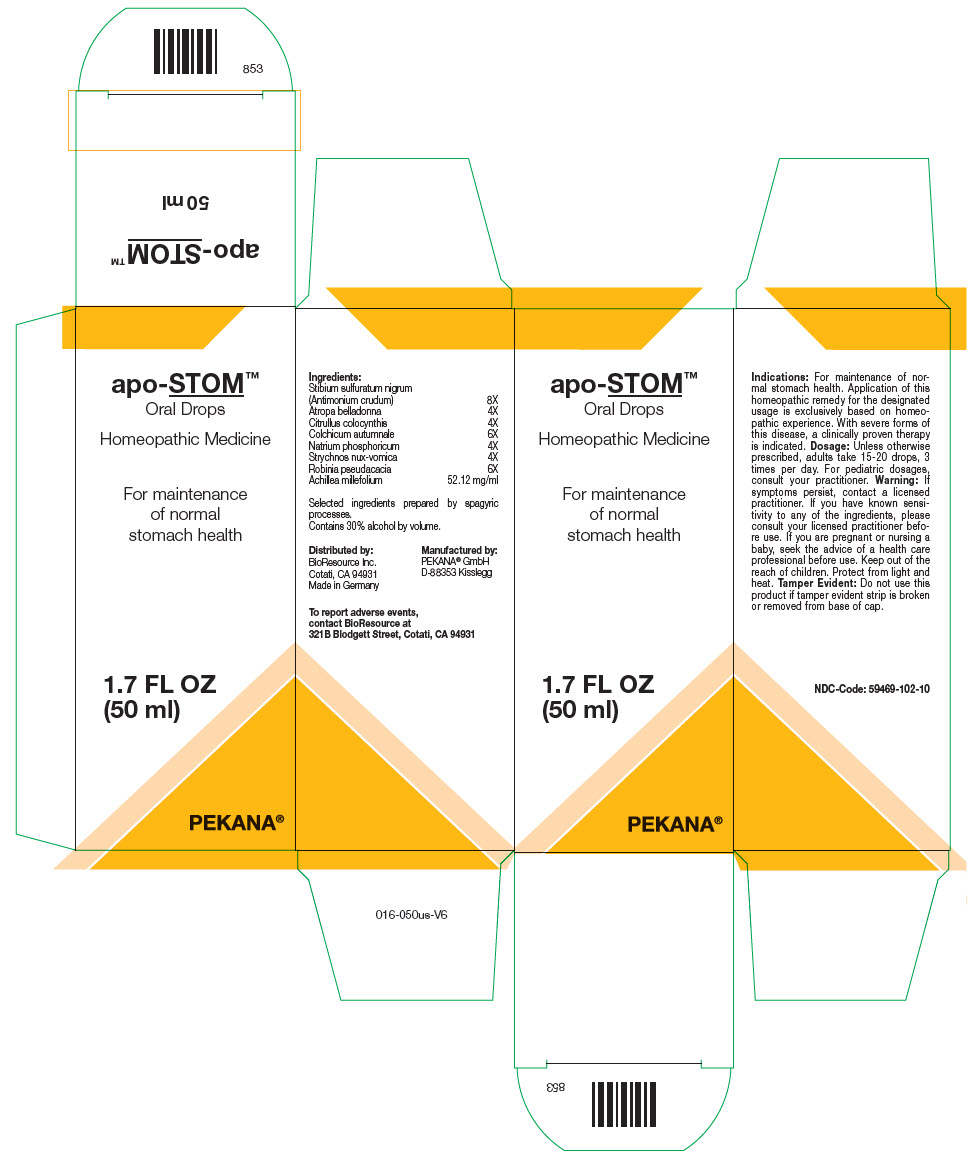 DRUG LABEL: apo-STOM
NDC: 59469-102 | Form: SOLUTION/ DROPS
Manufacturer: PEKANA Naturheilmittel GmbH
Category: homeopathic | Type: HUMAN OTC DRUG LABEL
Date: 20221206

ACTIVE INGREDIENTS: Antimony trisulfide 8 [hp_X]/50 mL; Atropa bella-donna Flowering Top 4 [hp_X]/50 mL; Colchicum autumnale Bulb 6 [hp_X]/50 mL; Citrullus colocynthis Fruit Pulp 4 [hp_X]/50 mL; Sodium phosphate 4 [hp_X]/50 mL; Strychnos nux-vomica Seed 4 [hp_X]/50 mL; Robinia pseudoacacia Bark 6 [hp_X]/50 mL; Achillea millefolium Flowering Top 2606 mg/50 mL
INACTIVE INGREDIENTS: Water; Alcohol

apo-STOM™

ACTIVE INGREDIENT

Ingredients:
Stibium sulfuratum nigrum (Antimonium crudum) | 8X
Atropa belladonna | 4X
Citrullus colocynthis | 4X
Colchicum autumnale | 6X
Natrium phosphoricum | 4X
Strychnos nux-vomica | 4X
Robinia pseudacacia | 6X
Achillea millefolium | 52.12 mg/ml

Selected ingredients prepared by spagyric processes.

INACTIVE INGREDIENT

Contains 30% alcohol by volume.

Indications

PURPOSE

For maintenance of normal stomach health. Application of this homeopathic remedy for the designated usage is exclusively based on homeopathic experience. With severe forms of this disease, a clinically proven therapy is indicated.

Dosage

Unless otherwise prescribed, adults take 15-20 drops, 3 times per day. For pediatric dosages, consult your practitioner.

Warning

If symptoms persist, contact a licensed practitioner. If you have known sensitivity to any of the ingredients, please consult your licensed practitioner before use. If you are pregnant or nursing a baby, seek the advice of a health care professional before use.

Keep out of the reach of children.

STORAGE AND HANDLING

Protect from light and heat.

Tamper Evident

Do not use this product if tamper evident strip is broken or removed from base of cap.

QUESTIONS

To report adverse events, contact BioResource at 321B Blodgett Street, Cotati, CA 94931

Distributed by:
BioResource Inc.
Cotati, CA 94931

Manufactured by:
PEKANA® GmbH
D-88353 Kisslegg

PRINCIPAL DISPLAY PANEL - 50 ml Bottle Box

apo-STOM™
Oral Drops

Homeopathic Medicine

For maintenance
of normal
stomach health

1.7 FL OZ
(50 ml)

PEKANA®